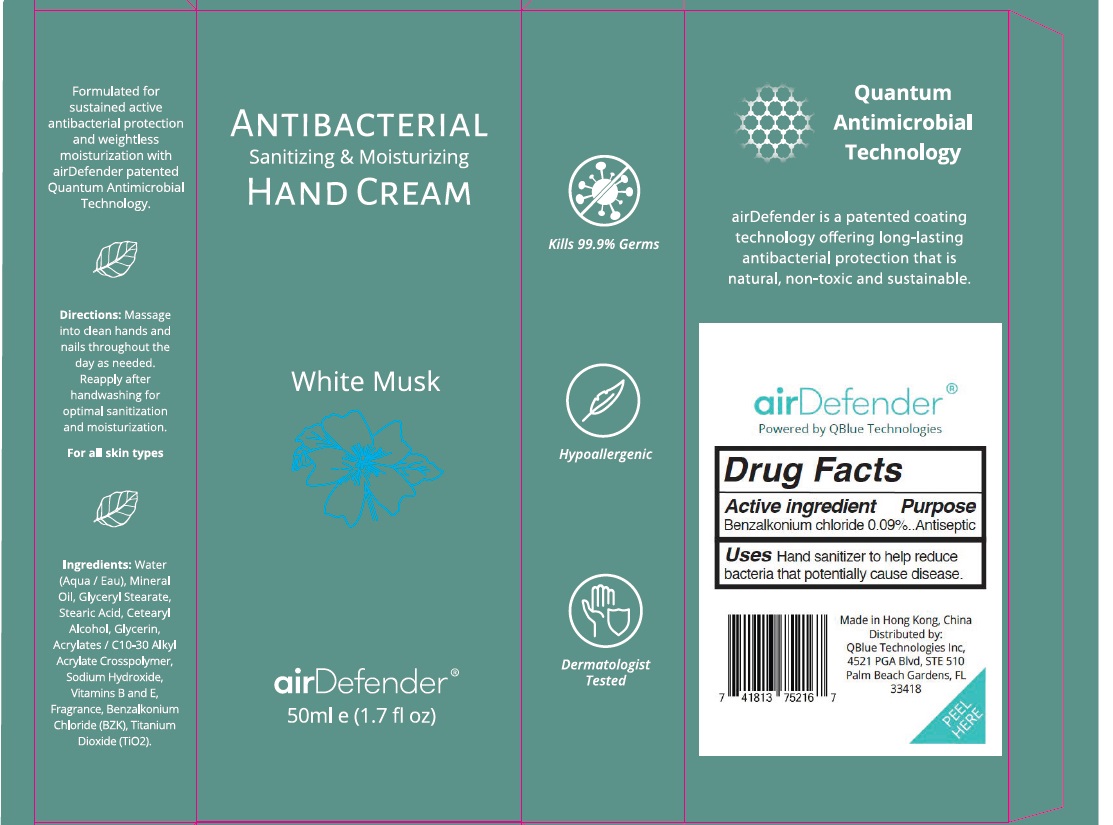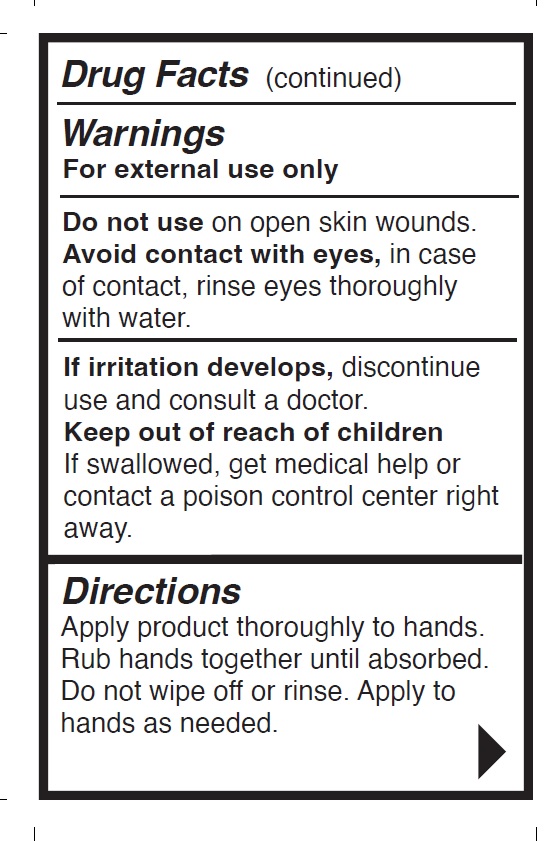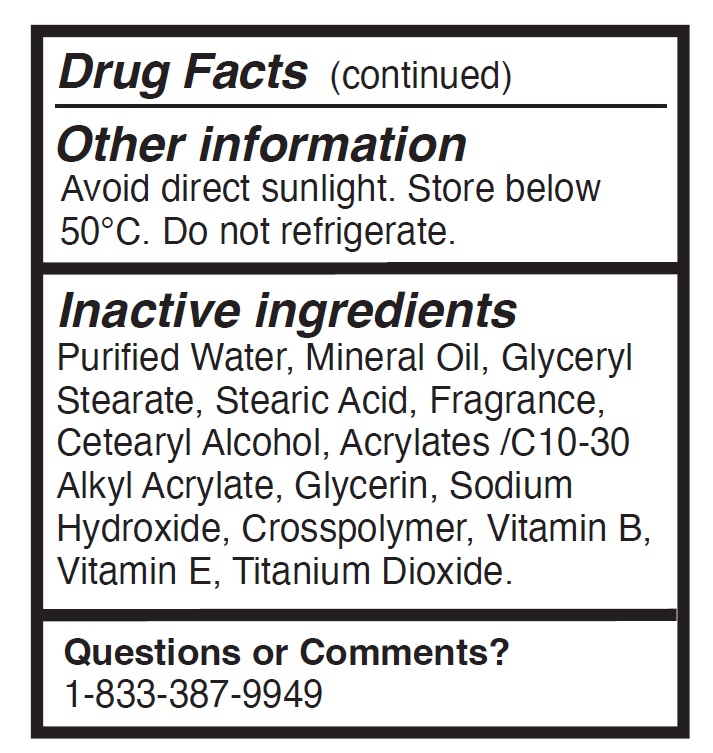 DRUG LABEL: ANTIBACTERIAL SANITIZING AND MOISTURIZING HAND
NDC: 83388-003 | Form: CREAM
Manufacturer: QBLUE TECHNOLOGIES, INC.
Category: otc | Type: HUMAN OTC DRUG LABEL
Date: 20230410

ACTIVE INGREDIENTS: BENZALKONIUM CHLORIDE 0.9 mg/1 mL
INACTIVE INGREDIENTS: CETOSTEARYL ALCOHOL; GLYCERIN; SODIUM HYDROXIDE; .ALPHA.-TOCOPHEROL; TITANIUM DIOXIDE; GLYCERYL STEARATE SE; STEARIC ACID; MINERAL OIL; WATER; CARBOMER COPOLYMER TYPE A

QBlue Hand Sanitizer Solution 50mL (83388-003-50)

Drug Facts - Active Ingredient

Benzalkonium Chloride 0.09%

Purpose

Antiseptic

Uses

Hand sanitizer to help reduce bacteria that potentially can cause disease.

Warnings

For external use only

Avoid contact with eyes.

In case of contact, rinse eyes thoroughly with water.

Do not Use

on open skin wounds.

If irritation develops

Discontinue use and consult a doctor.

Keep out of reach of children.

If swallowed, get medical help or contact poison control center right away.

Directions

Apply product thoroughly to hands.
Rub hands together until absorbed.
Do not wipe off or rinse. Apply to
hands as needed.

Other Information

Avoid direct sunlight. Store below
50°C. Do not refrigerate.

Inactive Ingredients

Purified Water, Mineral Oil, Glyceryl
Stearate, Stearic Acid, Fragrance,
Cetearyl Alcohol, Acrylates /C10-30
Alkyl Acrylate, Glycerin, Sodium
Hydroxide, Crosspolymer, Vitamin B,
Vitamin E, Titanium Dioxide.

Questions or comment?

1-833-387-9949

PDP

NDC: 83388-001-15